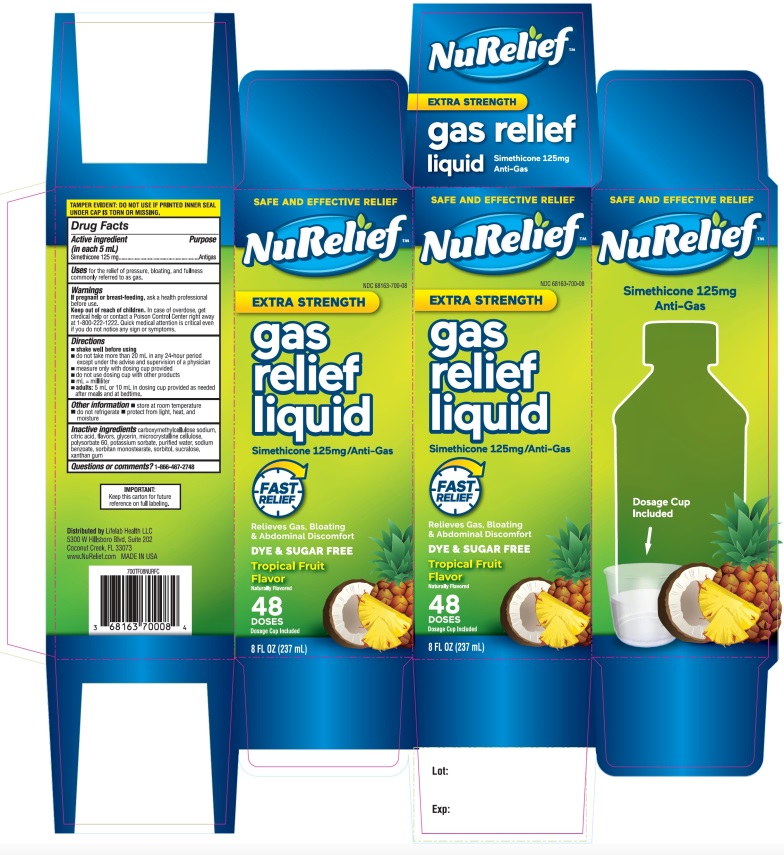 DRUG LABEL: EXTRA STRENGTH

NDC: 68163-700 | Form: LIQUID
Manufacturer: Raritan Pharmaceuticals Inc
Category: otc | Type: HUMAN OTC DRUG LABEL
Date: 20251014

ACTIVE INGREDIENTS: DIMETHICONE, UNSPECIFIED 125 mg/5 mL
INACTIVE INGREDIENTS: CARBOXYMETHYLCELLULOSE SODIUM, UNSPECIFIED; ANHYDROUS CITRIC ACID; GLYCERIN; MICROCRYSTALLINE CELLULOSE; POLYSORBATE 60; POTASSIUM SORBATE; WATER; SODIUM BENZOATE; SORBITAN MONOSTEARATE; SORBITOL; SUCRALOSE; XANTHAN GUM

NuRelief Extra Strength Gas Relief Liquid

Active Ingredient (in each 5 mL)

Simethicone 125 mg

Purpose

Antigas

Uses

for the relief of pressure, bloating, and fullness commonly referred to as gas

Warnings

If pregnant or breast-feeding,

ask a health professional before use.

Keep out of reach of children.

In case of overdose, get medical help or contact a Poison Control Center right away at 1-800-222-1222. Quick medical attention is critical even if you do not notice any sign or symptoms.

Directions

- shake well before using
- do not take more than 20 mL in any 24-hour period except under the advice and supervision of a physician
- measure only with dosing cup provided
- do not use dosing cup with other products
- mL = milliliter
- adults: 5 mL or 10 mL in dosing cup provided as needed after meals and at bedtime.
- do not exceed 4 soft gels in 24 hours unless directed by a doctor

Other information

- store at room temperature
- do not refrigerate
- protect from light, heat, and moisture

Inactive ingredients

carboxymethylcellulose sodium, citric acid, flavor, glycerin, microcrystalline cellulose, polysorbate 60, potassium sorbate, purified water, sodium benzoate, sorbitan monostearate, sorbitol, sucralose, xanthan gum.

Questions or comments?

Call 1-866-467-2748

Principal Display Panel

SAFE AND EFFECTIVE RELIEF

NuRelief™

NDC# 68163-700-08

Relieves Gas, Bloating & Abdominal Discomfort

EXTRA STRENGTH

Gas relief liquid

Simethicone 125mg/Anti-Gas

FAST RELIEF

Relives Gas, bloating & Abdominal Discomfort

DYE & SUGAR FREE

Tropical Fruit Flavor

Naturally Flavored

48 DOSES

Dosage cup Included

8 FL OZ (237 mL)

IMPORTANT:Keep this carton for future reference on full labeling.

Distributed by Lifelab Health LLC

5300 W Hillsboro Blvd, Suite 202

Coconut Creek, FL 33073

www.NuRelief.com

MADE IN USA

TAMPER EVIDENT: DO NOT USE IF CARTON IS OPENED OR IF BLISTER UNIT IS TORN, BROKEN OR SHOWS ANY SIGNS OF TAMPERING.